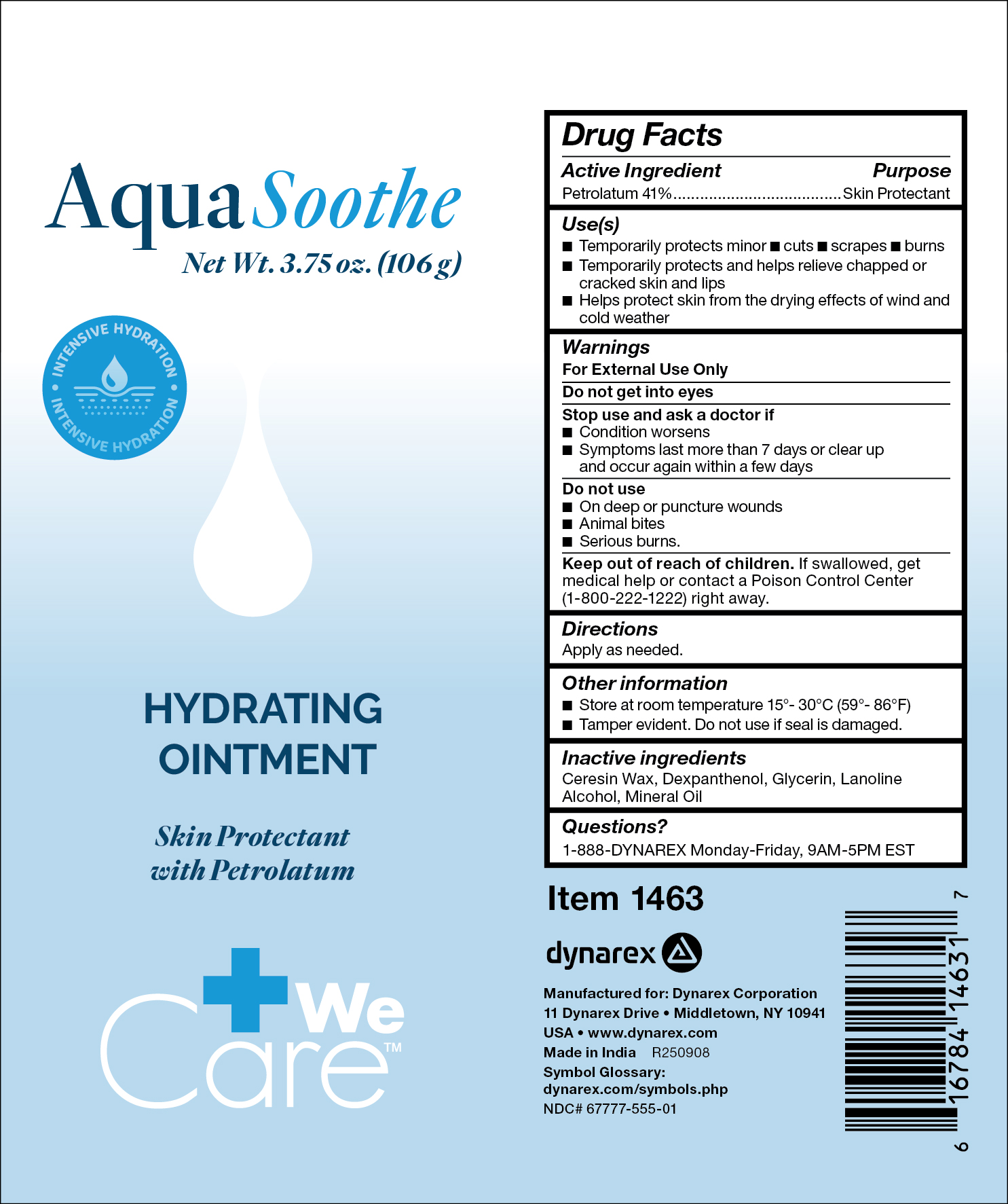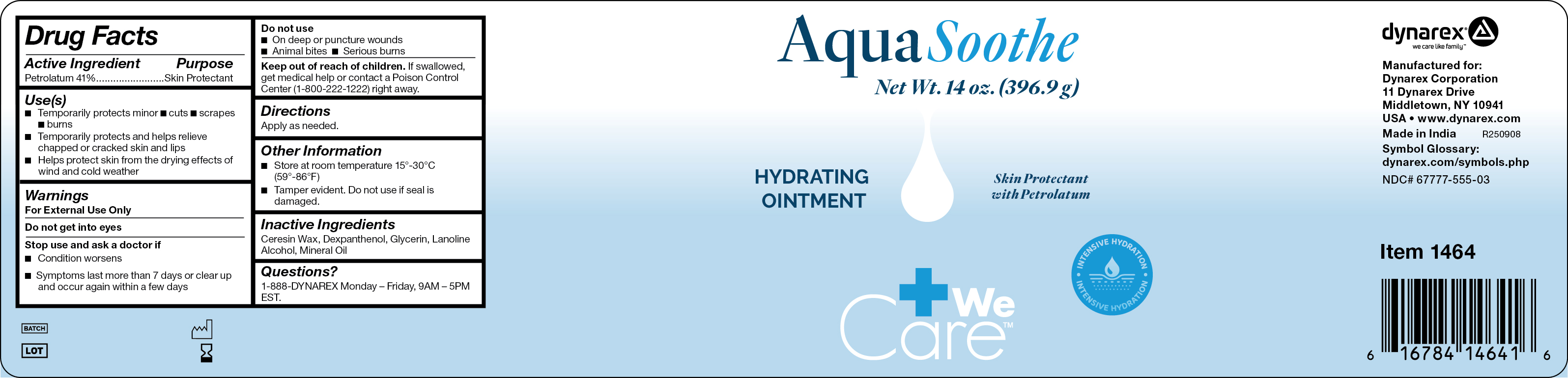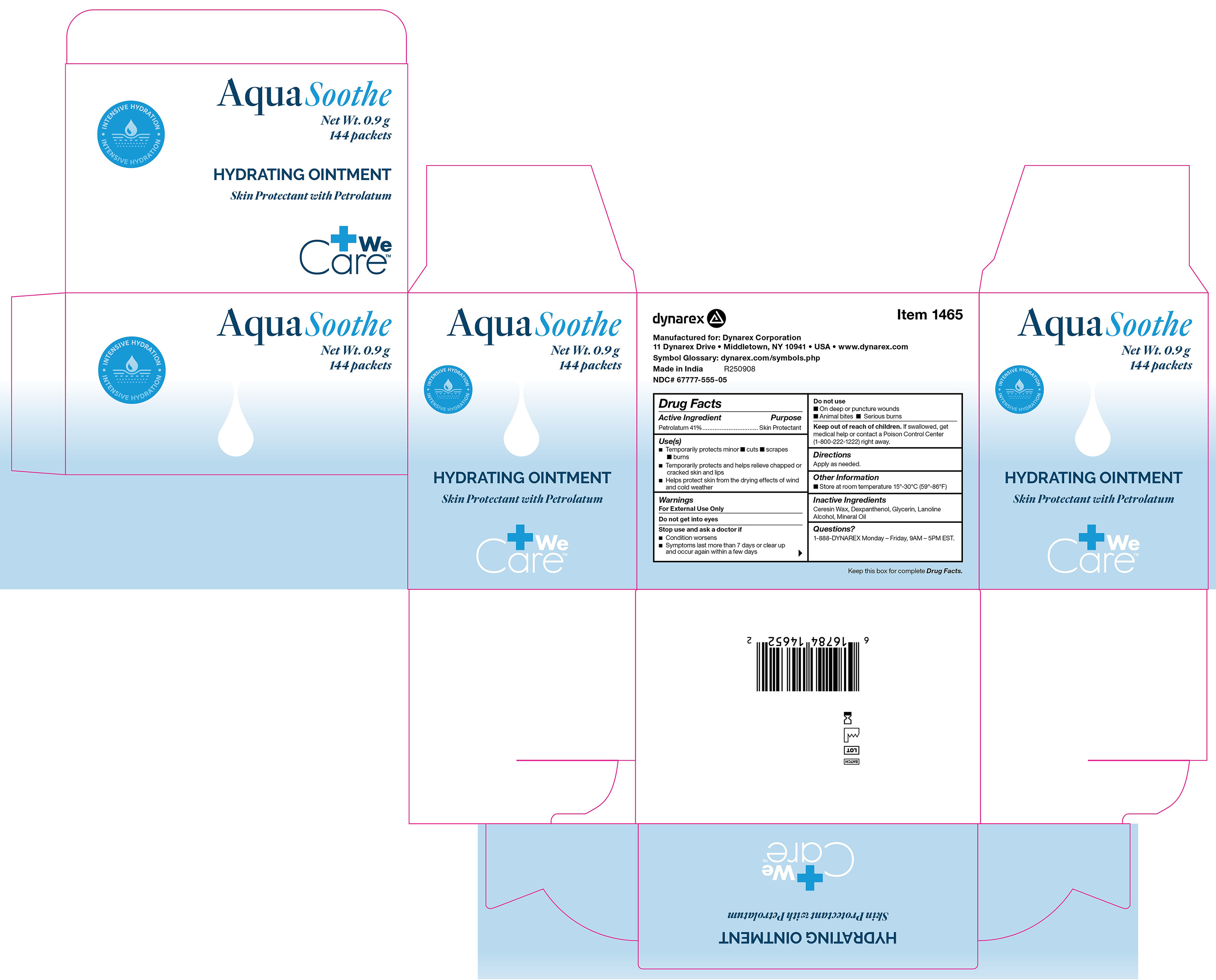 DRUG LABEL: AquaSoothe
NDC: 67777-555 | Form: OINTMENT
Manufacturer: Dynarex Corporation
Category: otc | Type: HUMAN OTC DRUG LABEL
Date: 20251209

ACTIVE INGREDIENTS: PETROLATUM 41 g/100 g
INACTIVE INGREDIENTS: MINERAL OIL; LANOLIN ALCOHOLS; DEXPANTHENOL; GLYCERIN; CERESIN

1463 AquaSoothe
1464 Aqua Soothe
1465 Aqua Soothe

Active ingredient

Petrolatum 41%

Purpose

Skin Protectant

Uses

• Temporarily protects minor • cuts • scrapes • burns

• Temporarily protects and helps relieve chapped or cracked skin and lips

• Helps protect skin from the drying effects of wind and cold weather

Warnings

For external use only

Do not get into eyes

Stop use and ask a doctor if

• Condition worsens

• Symptoms last more than 7 days or clear up and occur again with a few days

Do not use

• On deep or puncture wounds • Animal bites • Serious burns

Keep out of reach of children

If swallowed, get medical help or contact a Poison Control Center (1-800-222-1222) right away.

Other information

• Store at room temperature 15º - 30ºC (59º - 86ºF)

Directions

Apply as needed

Inactive ingredients

ceresin wax, dexpanthenol, glycerin, lanoline alcohol, mineral oil

Questions?

1-888-DYNAREX Monday - Friday 9AM - 5PM EST

Label

1465 Label

Label

1464 Label

Label

1463 Label